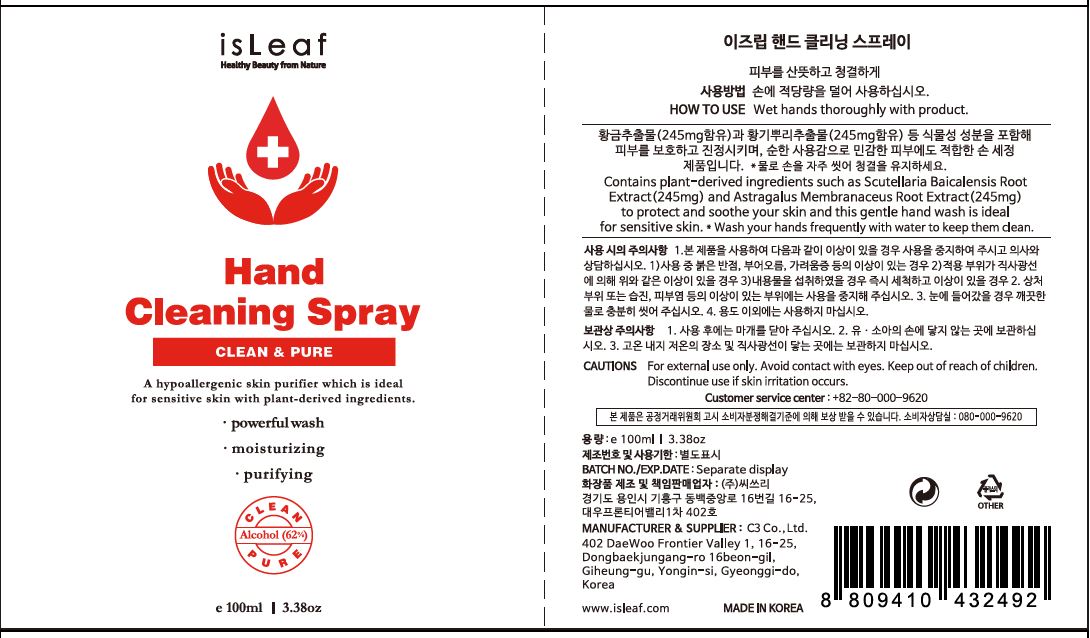 DRUG LABEL: isLeaf Hand Cleaning
NDC: 70818-024 | Form: SPRAY
Manufacturer: C3 Co., Ltd.
Category: otc | Type: HUMAN OTC DRUG LABEL
Date: 20200406

ACTIVE INGREDIENTS: ALCOHOL 65.3 g/100 mL
INACTIVE INGREDIENTS: WATER

C3 Co., Ltd. - isLeaf Hand Cleaning Gel

ACTIVE INGREDIENT

Alcohol

INACTIVE INGREDIENT

Water
Astragalus Membranaceus Root Extract
Eclipta Prostrata Extract
Scutellaria Baicalensis Root Extract
Morus Alba Bark Extract
1,2-Hexanediol
Lavandula Angustifolia (Lavender) Oil
PPG-26-Buteth-26
PEG-40 Hydrogenated Castor Oil
Water
Glycerin
Undecylenoyl Glycine
Undecylenic Acid

PURPOSE

Antiseptic

keep out of reach of the children

INDICATIONS AND USAGE

Wet hands thoroughly with product

WARNINGS

For external use only.

Avoid contact with eyes.

Keep out of reach of children.

Discontinue use if skin irritation occurs.

DOSAGE AND ADMINISTRATION

for external use only